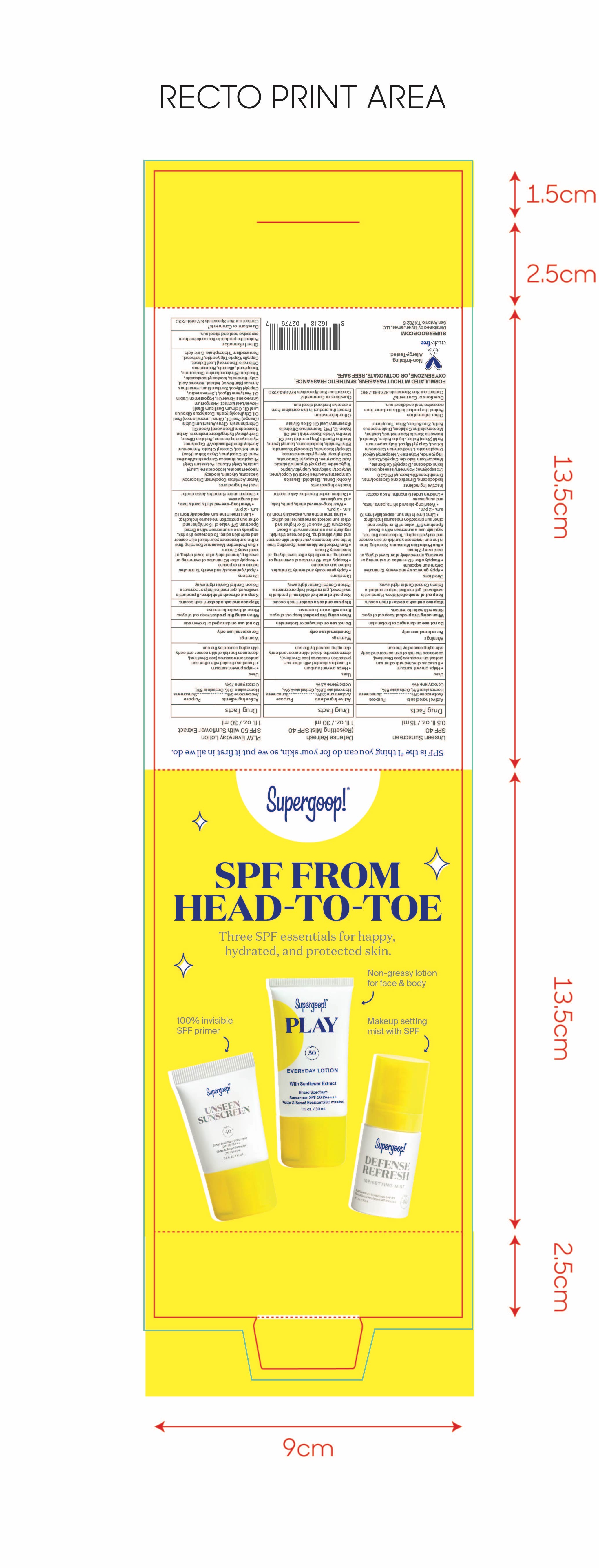 DRUG LABEL: Head to Toe Kit
NDC: 82384-0001 | Form: KIT | Route: TOPICAL
Manufacturer: System Beauty, LLC
Category: otc | Type: HUMAN OTC DRUG LABEL
Date: 20211206

ACTIVE INGREDIENTS: OCTISALATE 5 g/100 mL; HOMOSALATE 8 g/100 mL; OCTOCRYLENE 4 g/100 mL; AVOBENZONE 3 g/100 mL; AVOBENZONE 2.8 g/100 mL; HOMOSALATE 9.8 g/100 mL; OCTISALATE 4.9 g/100 mL; OCTOCRYLENE 9.5 g/100 mL; OCTOCRYLENE 7.5 g/100 mL; AVOBENZONE 3 g/100 mL; OCTISALATE 5 g/100 mL; HOMOSALATE 10 g/100 mL
INACTIVE INGREDIENTS: DICAPRYLYL CARBONATE; MICROCRYSTALLINE CELLULOSE; POLYMETHYLSILSESQUIOXANE (4.5 MICRONS); SILICON DIOXIDE; ISODODECANE; DIATOMACEOUS EARTH; ZINC SULFATE; DIMETHICONE CROSSPOLYMER (450000 MPA.S AT 12% IN CYCLOPENTASILOXANE); LECITHIN, SOYBEAN; INDIAN FRANKINCENSE; PHYMATOLITHON CALCAREUM; CAPRYLYL GLYCOL; SHEA BUTTER; MANNITOL; POLYESTER-7; MEDIUM-CHAIN TRIGLYCERIDES; NEOPENTYL GLYCOL DIHEPTANOATE; DIMETHICONE/BIS-ISOBUTYL PPG-20 CROSSPOLYMER; ISOHEXADECANE; TOCOPHEROL; POVIDONE, UNSPECIFIED; ISODODECANE; SPEARMINT OIL; LEVOMENOL; BUTYLOCTYL SALICYLATE; DIHEPTYL SUCCINATE; MEDIUM-CHAIN TRIGLYCERIDES; LAUROYL LYSINE; CAPRYLOYL GLYCERIN/SEBACIC ACID COPOLYMER (2000 MPA.S); DICAPRYLYL CARBONATE; DIETHYLHEXYL SYRINGYLIDENEMALONATE; ALCOHOL; ETHYL FERULATE; PEPPERMINT OIL; NYLON-12; ROSEMARY OIL; CITRIC ACID MONOHYDRATE; PELARGONIUM GRAVEOLENS FLOWER OIL; POGOSTEMON CABLIN LEAF OIL; PENTYLENE GLYCOL; ALLANTOIN; LEMON OIL, COLD PRESSED; EUCALYPTUS OIL; HELIANTHUS ANNUUS FLOWERING TOP; BEHENIC ACID; CETYL BEHENATE; RICE BRAN; CETEARYL OLIVATE; ROSEWOOD OIL; CHLORPHENESIN; ROSEMARY; MEDIUM-CHAIN TRIGLYCERIDES; SODIUM TRIPOLYPHOSPHATE ANHYDROUS; BUTYL ACRYLATE/METHYL METHACRYLATE/METHACRYLIC ACID COPOLYMER (18000 MW); DIISOPROPYL SEBACATE; 1,2-HEXANEDIOL; CAPRYLYL GLYCOL; XANTHAN GUM; ISOSTEARYL ISOSTEARATE; TOCOPHEROL; ISODECYL NEOPENTANOATE; ISODODECANE; CETYL ALCOHOL; POTASSIUM CETYL PHOSPHATE; AMMONIUM ACRYLOYLDIMETHYLTAURATE/VP COPOLYMER; HYDROXYACETOPHENONE; DIETHYLHEXYL SYRINGYLIDENEMALONATE; SORBITAN OLIVATE; PANTHENOL; LAURYL LACTATE; ORANGE OIL, COLD PRESSED; OCIMUM BASILICUM FLOWERING TOP; WATER; GLYCERIN; ETHYLHEXYLGLYCERIN; TRISODIUM ETHYLENEDIAMINE DISUCCINATE

Head-to-Toe Kit

Play Everyday Sunscreen SPF 50 with Sunflower extract Active ingredients

Active Ingredients Purpose

Avobenzone 3% Sunscreen

Homosalate 10% Sunscreen

Octisalate 5% Sunscreen

Octocrylene 7.5% Sunscreen

Defense Refresh (Re)setting Mist SPF 40

ACTIVE INGREDIENT PURPOSE

Avobenzone 2.8%..............Sunscreen

Homosalate 9.8%.............Sunscreen

Octisalate 4.9%..................Sunscreen

Octocrylene 9.5%...............Sunscreen

Unseen Sunscreen SPF 40 active ingredients

Active Ingredients Purpose

Avobenzone 3% Sunscreen

Homosalate 8% Sunscreen

Octocrylene 4% Sunscreen

Octisalate 5% Sunscreen

Uses

Helps Prevent Sunburn

If used as directed with other sun protection measures (see Directions), decreases the risk of Skin cancer and early skin aging caused by the sun

Keep out of reach of children. If swallowed, get medical help or contact a Poison Control Center right away

Stop use and ask a doctor if rash occurs

Warnings

For External use only

Do not use on damaged or broken skin

When using this product, Keep out of eyes. Rinse with water to remove

Play Everyday Lotion SPF 50 with Sunflower Extract Directions

Directions

- Apply generously and evenly 15 minutes before sun exposure
- Reapply:after 80 minutes of swimming or sweating

immediately after towel drying
at least every 2 hours

- Sun Protection Measures. Spending time in the sun increases your risk of skin

cancer and early skin aging. To decrease this risk, regularly use a sunscreen
with broad spectrum SPF of 15 or higher and other sun protection measures
including:

- limit time in the sun, especially from 10 a.m. - 2 p.m.
- Wear Long-sleeved shirts, pants, hats, and sunglasses
- Children under 6 months: Ask a doctor

Directions

- Apply generously and evenly 15 minutes before sun exposure
- Reapply:after 40 minutes of swimming or sweating

immediately after towel drying
at least every 2 hours

- Sun Protection Measures. Spending time in the sun increases your risk of skin

cancer and early skin aging. To decrease this risk, regularly use a sunscreen
with broad spectrum SPF of 15 or higher and other sun protection measures
including:

- limit time in the sun, especially from 10 a.m. - 2 p.m.
- Wear Long-sleeved shirts, pants, hats, and sunglasses
- Children under 6 months: Ask a doctor

Unseen Sunscreen SPF 40 Inactive Ingredients

Inactive Ingredients

Isododecane, Dimethicone Crosspolymer, Dimethicone/Bis-Isobutyl PPG-20 Crosspolymer, Polymethylsilsesquioxane, Isohexadecane, Dicrapylyl Carbonate, Meadowfoam Estolide, Caprylic/Capric Triglyceride, Polyester-7, Neopentyl Glycol Diheptanoate, Lithothamnion Calcareum Extract,Butyrospermum Parkii (Shea) Butter, Jojoba Esters, Mannitol, Boswellia Serrata Resin Extract, Lecithin, Microcrystalline Cellulose, Diatomaceous Earth, Zinc Sulfate, Silica, Tocopherol

Defense Refresh (Re)setting Mist SPF 40 Inactive Ingredients

Inactive Ingredients

Alcohol Denat., Bisabolol, Brassica Campestris/Aleurites Fordi Oil Copolymer, Butyloctyl Salicylate, Caprylic/Capric Triglyceride, Capryloyl Glycerin/Sebacic Acid Copolymer, Dicaprylyl Carbonate, Diethylhexyl Syringylidenemalonate, Diheptyl Succinate, Diisooctyl Succinate, Ethyl Ferulate, Isododecane, Lauroyl Lysine, Mentha Piperita (Peppermint) Oil, Mentha Viridis (Spearmint) Leaf Oil, Nylon-12, PVP, Rosmarinus Officinalis (Rosemary) Leaf Oil, Silica Silylate

Play Everyday Sunscreen SPF 50 with sunflower Inactive ingredients

Inactive ingredients

Water, Acrylates Copolymer, Diisopropyl Sebacate, Glycerin, Isodecyl Neopentanoate, Isododecane, Lauryl Lactate, Cetyl Alcohol, Potassium Cetyl Phosphate, Brassica Camprestris/Aleurites Fordi Copolymer, Oryza Sativa (Rice) Bran Extract, Cetearyl Olivate, Ammonium Acryloyldimethyltaurate/VP Copolymer, Hydroxyacetophenone, Sorbitan Olivate, Diethylhexyl Syringylidenemalonate, Aniba Rosaeodora (Rosewood) Wood Oil, Chlorphenesin, Citrus Aurantium Dulcis (Orange) Peel Oil, Citrus Limon (Lemon) Peel Oil, Ethylhexylglycerin, Eucalyptus Globulus Leaf Oil, Ocimum Bascilicum (Basil) Flower/Leaf Extract, Pelargonium Graveolens Flower Oil, Pogostemon Cablin Oil, Pentylene Glycol, 1,2-hexanediol, Caprylyl Glycol, Xanthan Gum, Helianthus Annuus (Sunflower) Extract, Behenic Acid, Cetyl Behenate, Isostearyl Isostearate, Trisodium Ethylenediamene Disuccinate, Tocopherol, Allantoin, Rosmarinus Officinalis (Rosemary) Leaf Extract, Caprylic/Capric Triglyceride,Panthenol, Pentasodium Triphosphate, Citric Acid

PACKAGE LABEL

Supergoop!

SPF FROM HEAD TO TOE

Three SPF essentials for happy, hydrated, and protected skin

Unseen Sunscreen SPF 40

0.5 fl.oz./ 15 ml

Defense Refresh (Re)setting Mist SPF 40

1 fl. oz. / 30 ml

Play Everyday Lotion SPF 50 with Sunflower Extract

1 fl. oz. / 30 ml